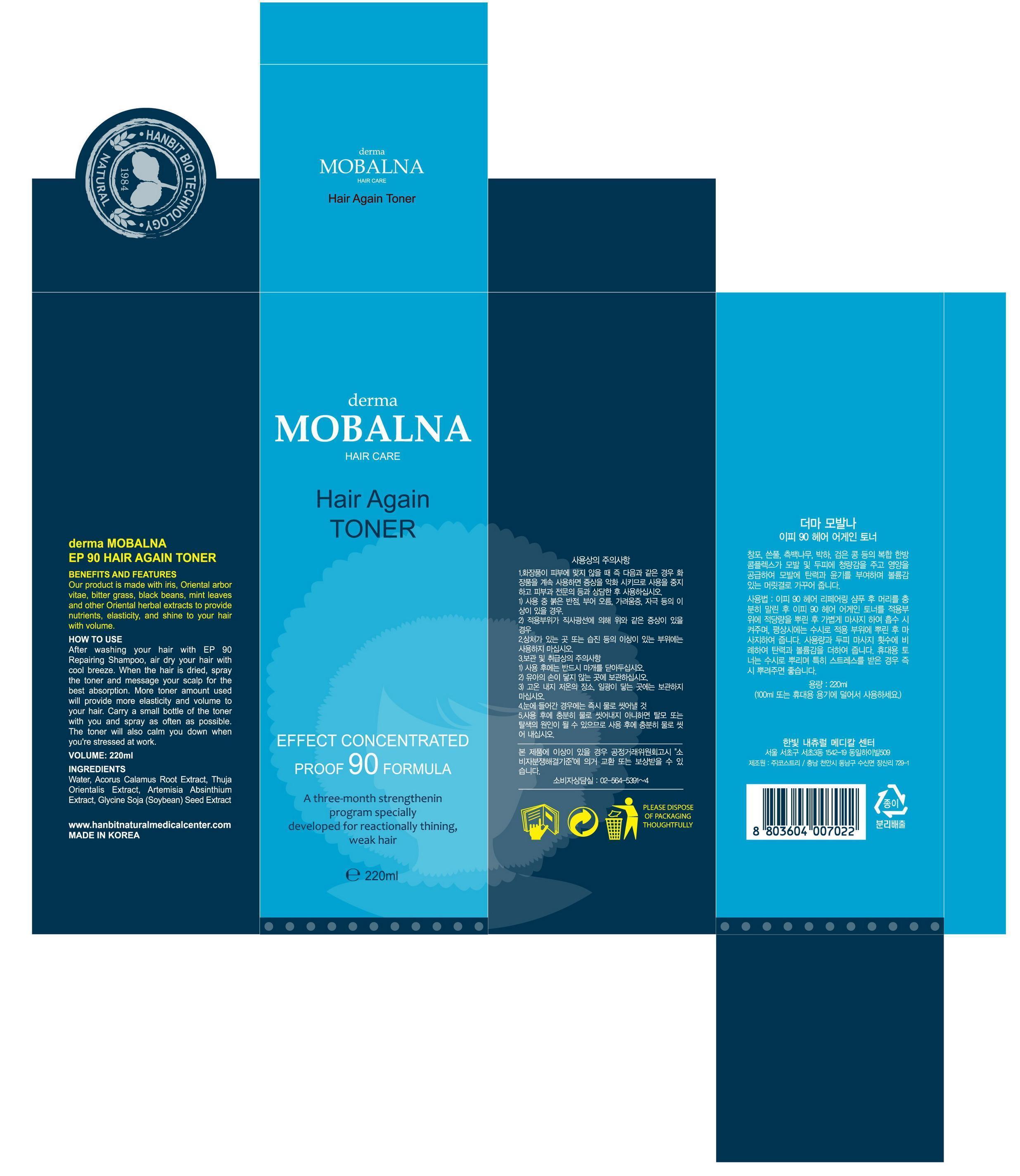 DRUG LABEL: derma MOBALNA EP 90 Hair Again Toner
NDC: 51329-2001 | Form: LIQUID
Manufacturer: Hanbit Korea
Category: otc | Type: HUMAN OTC DRUG LABEL
Date: 20140330

ACTIVE INGREDIENTS: ACORUS CALAMUS ROOT 0.15 g/1 mL
INACTIVE INGREDIENTS: WATER; PLATYCLADUS ORIENTALIS LEAF; WORMWOOD; CITRUS PARADISI FRUIT OIL; SOYBEAN

Drug Facts

ACTIVE INGREDIENT

Acorus Calamus Root Extract

INACTIVE INGREDIENT

water, thuja orientalis ext, artemisia absinthium ext, soybean seed ext, grapefruit fruit ext

PURPOSE

1. You will have volumized hair.
2. There will be less hair loss during hair care such as shampooing.
3. When the pores on your scalp open, you may feel itchy. This is the sign of new hair rowth.

KEEP OUT OF REACH OF CHILDREN

Keep this product out of the reach of children

INDICATIONS AND USAGE

1. Wash your hair with lukewarm water and wait for previously applied toner to absorb into the pores.
2. Make a lot of foam using Mobalna soap and massage your scalp for about 5-7 minutes. Rinse with lukewarm water.
3. Massaging stimulates and accelerates the pores to open and allow Mobalna to be absorbed.
4. After thoroughly drying your hair (do not hot air dry), apply appropriate amount of Mobalna toner.
5. When you apply Mobana toner after a haircut, make sure to massage your scalp or to comb your hair at night to improve absorption.
6. Applying Mobalna toner on your eyebrows will also make your eyesbrows darker and healthier.
7. If you are a first time Mobalna user, use it as frequently as possible. If you are stressing out from work or school, spray the toner regularly to cool your head. Rise of the temperature caused by stress may accelerate hair loss. That is why washing or drying hair in hot temperature should be voided.

WARNINGS

1.avoid direct contact with the eyes, mucous membranes and open wounds. 2. If redness or imitation occurs, discontinue use and consult with your physician.3. Keep this product out of the reach of children.

DOSAGE AND ADMINISTRATION

for external use only